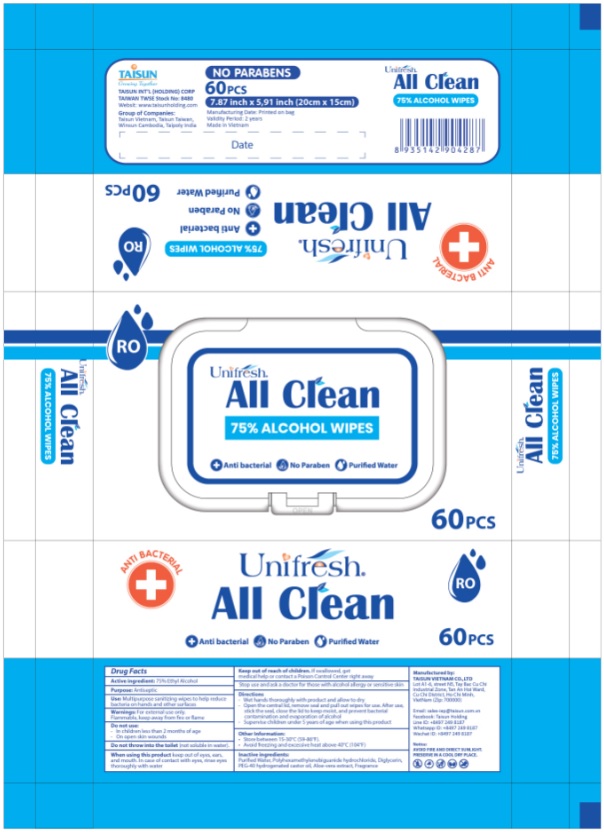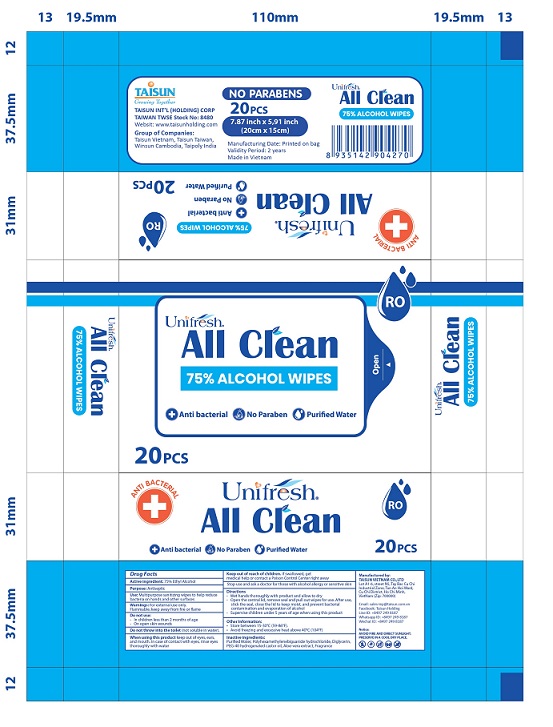 DRUG LABEL: Unifresh All Clean alcohol
NDC: 80493-102 | Form: CLOTH
Manufacturer: TAISUN VIETNAM CO.,LTD
Category: otc | Type: HUMAN OTC DRUG LABEL
Date: 20201112

ACTIVE INGREDIENTS: ALCOHOL 75 mL/100 1
INACTIVE INGREDIENTS: POLYOXYL 40 HYDROGENATED CASTOR OIL; ALOE VERA LEAF; WATER; POLIHEXANIDE HYDROCHLORIDE; DIGLYCERIN

ACTIVE INGREDIENT

Alcohol 75%

INACTIVE INGREDIENT

Water, Polyhexamethylenebiguanide hydrochloride, Diglycerin, PEG-40 hydrogenated castor oil, Aloe-vera extract, Fragrance

PURPOSE

Antiseptic

INDICATIONS AND USAGE

Used for antibacterial hand skin, prevent bacteria.

WARNINGS

For external use only. Flammable. Keep away from fire.

DO NOT USE

• Keep away from fire.
• Do not wipe your eyes.
• Do not throw into the toilet (not soluble in water).

WHEN USING

• Please wait until the alcohol has completely evaporated after wiping.
• Before use, check whether the packaging is intact. Do not use if it is damaged.

Stop use and ask a doctor for those with alcohol allergy or sensitive skin.

Keep out of reach of children.

STORAGE AND HANDLING

• Store between 15-30°C (59-86°F).
• Avoid freezing and excessive heat above 40°C (104°F).

DOSAGE AND ADMINISTRATION

Use it as needed, after following the usage instructions. For external use only

PACKAGE LABEL

Unifresh All Clean Hand Sanitizer Wipes_60pcs

Unifresh All Clean Hand Sanitizer Wipes_20pcs